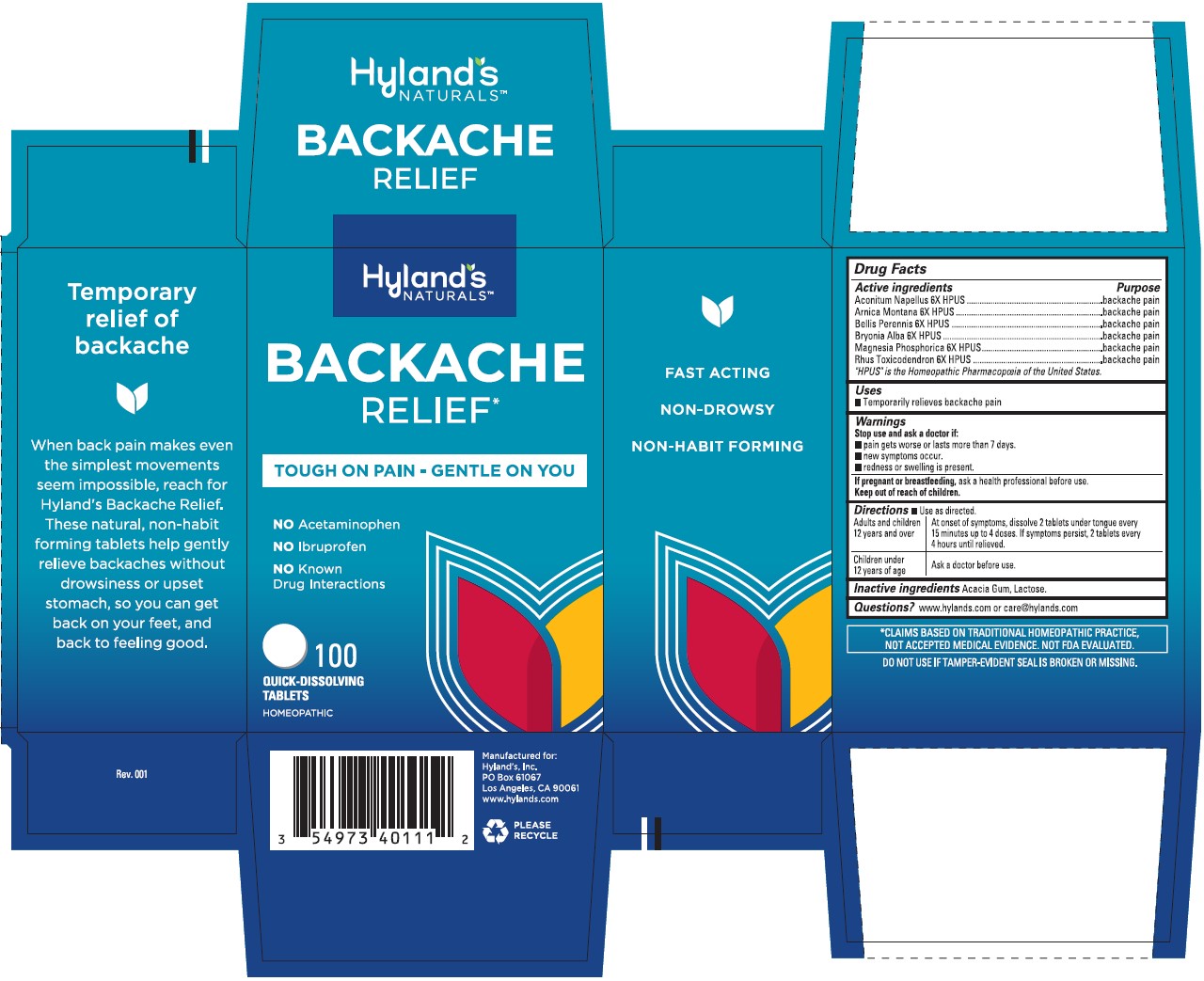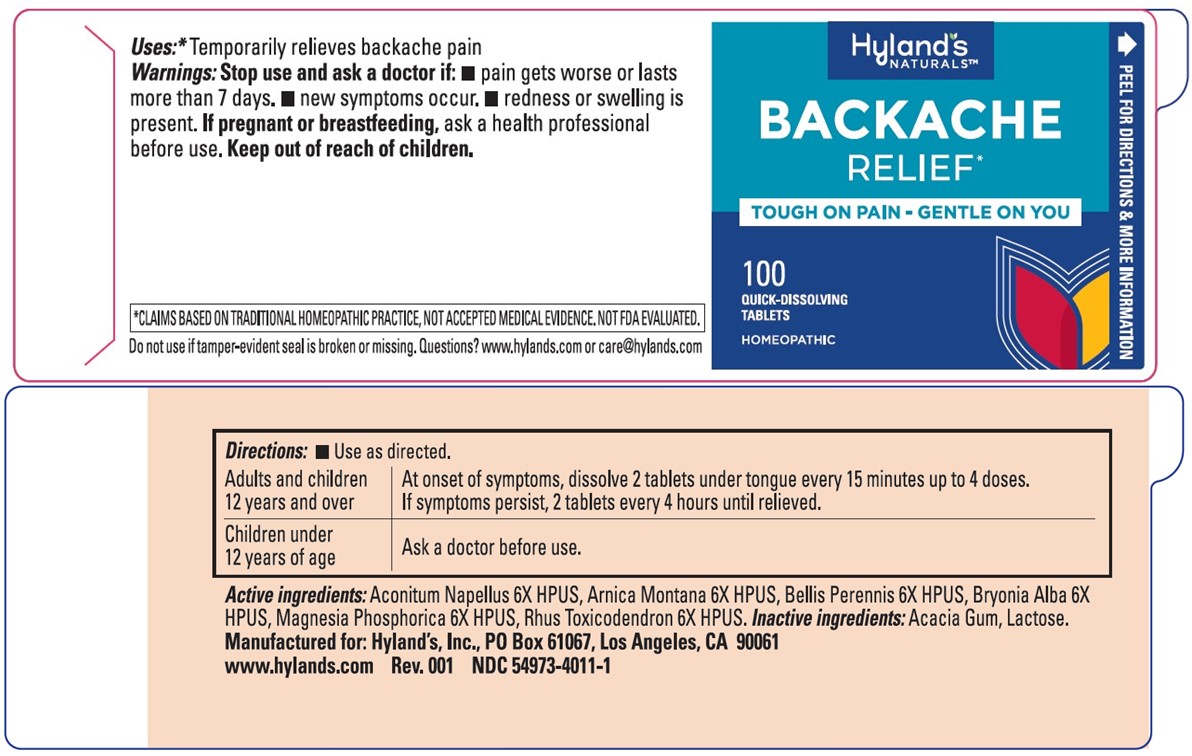 DRUG LABEL: Backache Relief
NDC: 54973-4011 | Form: TABLET
Manufacturer: Hyland's Inc.
Category: homeopathic | Type: HUMAN OTC DRUG LABEL
Date: 20230510

ACTIVE INGREDIENTS: ARNICA MONTANA 6 [hp_X]/1 1; BELLIS PERENNIS 6 [hp_X]/1 1; ACONITUM NAPELLUS 6 [hp_X]/1 1; BRYONIA ALBA ROOT 6 [hp_X]/1 1; MAGNESIUM PHOSPHATE, DIBASIC TRIHYDRATE 6 [hp_X]/1 1; TOXICODENDRON PUBESCENS LEAF 6 [hp_X]/1 1
INACTIVE INGREDIENTS: LACTOSE MONOHYDRATE; ACACIA

Hyland's Naturals Backache Relief

PURPOSE

Backache Relief

Drug Facts

Active ingredients

Active ingredients | Purpose
Aconitum Napellus 6X HPUS | backache pain
Arnica Montana 6X HPUS | backache pain
Bellis Perennis 6X HPUS | backache pain
Bryonia Alba 6X HPUS | backache pain
Magnesia Phosphorica 6X HPUS | backache pain
Rhus Toxicodendron 6X HPUS | backache pain

"HPUS" indicates that the active ingredients are in the official Homeopathic

Pharmacopoeia of the United States.

Uses

■ Temporarily relieves backache pain

Warnings

Stop use and ask a doctor if

■ pain gets worse or lasts more than 7 days.
■ new symptoms occur.
■ redness or swelling is present

If pregnant or breastfeeding

Ask a health professional before use.

Directions

■ Use as directed.

Adults and children 12 years and over | At onset of symptoms, dissolve 2 tablets under tongue every; 15 minutes up to 4 doses. If symptoms persist, 2 tablets every; 4 hours until relieved.
Children under 12 years of age | Ask a doctor before use.

Inactive ingredients

Acacia Gum, Lactose.

Questions?

www.hylands.com or care@hylands.com

Dosage and Administration

(Directions)

■ Use as directed

Adults and children 12 years and over | At onset of symptoms, dissolve 2 tablets under tongue every 15 minutes up to 4 doses. If symptoms persist, 2 tablets every 4 hours until relieved.
Children under 12 years of age | Ask a doctor before use.

Indications and Usage

Uses

■ Helps temporarily relieve backache pain

Removed "Helps"

Principal Display Panel

NDC 54973-4011-1

100 TABLETS